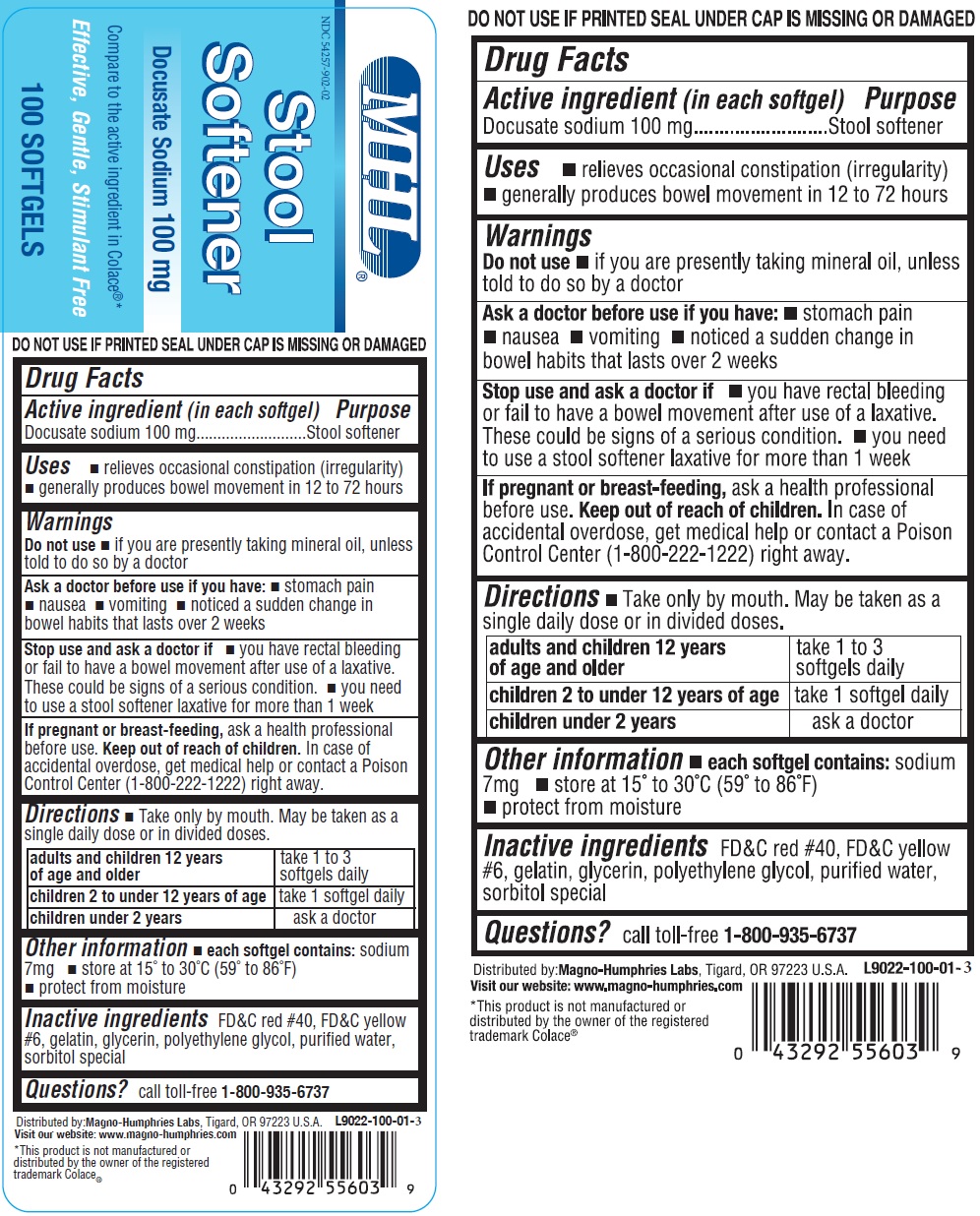 DRUG LABEL: Stool Softener Docusate Sodium
NDC: 54257-902 | Form: CAPSULE, GELATIN COATED
Manufacturer: Magno-Humphries, Inc.
Category: otc | Type: HUMAN OTC DRUG LABEL
Date: 20231027

ACTIVE INGREDIENTS: DOCUSATE SODIUM 100 mg/1 1
INACTIVE INGREDIENTS: FD&C YELLOW NO. 6; FD&C RED NO. 40; GELATIN; GLYCERIN; POLYETHYLENE GLYCOL, UNSPECIFIED; WATER

Stool Softener Docusate Sodium

Active ingredient (in each softgel)

Docusate sodium 100 mg

Purpose

Stool softener

Uses

- relieves occasional constipation (irregularity)
- generally produces bowel movement in 12 to 72 hours

Warnings

Do not use

- if you are presently taking mineral oil, unless told to do so by a doctor

Ask a doctor before use if you have

- stomach pain
- nausea
- vomiting
- noticed a sudden change in bowel habits that lasts over 2 weeks

Stop use and ask a doctor if

- you have rectal bleeding or fail to have a bowel movement after use of a laxative. These could be signs of a serious condition.
- you need to use a stool softener laxative for more than 1 week

If pregnant or breast-feeding,

ask a health professional before use.

Keep out of reach of children.

In case of accidental overdose, get medical help or contact a Poison Control Center (1-800-222-1222) right away.

Directions

- Take only by mouth. Doses may be taken as a single daily dose, preferably in the evening, or in divided doses.

adults and children 12 years of age and older | take 1 to 3 softgels daily
children 2 to under 12 years of age | take 1 softgel daily
children under 2 years | ask a doctor

Other information

- ach softgel contains: sodium 7mg
- store at 15° to 30°C (59° to 86°F)
- protect from moisture

Inactive ingredients

FD&C red #40, FD&C yellow #6, gelatin, glycerin, polyethylene glycol, purified water, sorbitol special

Questions?

call toll-free 1-800-935-6737